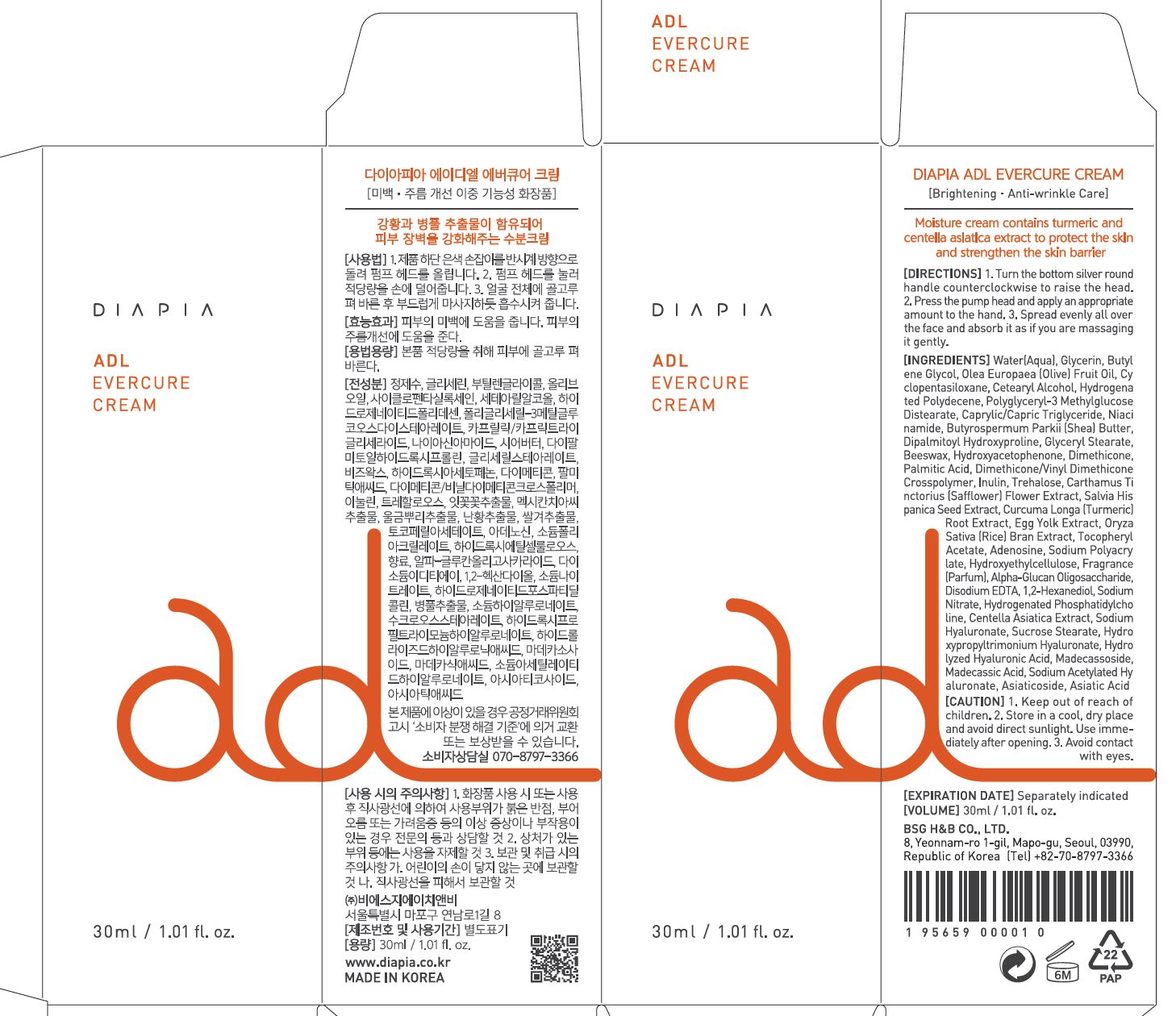 DRUG LABEL: DIAPIA ADL EvercureCream
NDC: 71857-0016 | Form: CREAM
Manufacturer: BSG H & B Co., Ltd.
Category: otc | Type: HUMAN OTC DRUG LABEL
Date: 20211201

ACTIVE INGREDIENTS: ADENOSINE 0.04 g/100 mL; NIACINAMIDE 2 g/100 mL
INACTIVE INGREDIENTS: WATER

Drug Facts

ACTIVE INGREDIENT

Niacinamide

INACTIVE INGREDIENT

Water
Glycerin
Centella Asiatica Extract
Hydrogenated Polydecene
1,2-Hexanediol
Butylene Glycol
Cetearyl Alcohol
Polyacrylate-13
Polyisobutene
Polysorbate 20
Polysorbate60
C13-14 Isoparaffin
Dimethicone
Sodium Polyacrylate
Simmondsia Chinensis (Jojoba)
Seed Oil
Olea Europaea (Olive) Fruit Oil
Helianthus Annuus (Sunflower)
Seed Oil
Betaine
Macadamia Ternifolia Seed Oil
Acrylates/C10-30 Alkyl Acrylate Crosspolymer
Phenoxyethanol
Xanthan Gum
Triethanolamine
Disodium EDTA
Curcuma Longa (Turmeric)
Root Powder
Curcuma Longa (Turmeric) Root Extract
Portulaca Oleracea Extract

PURPOSE

Brightening, anti wrinkle care

keep out of reach of the children

INDICATIONS AND USAGE

apply an appropriate amount to the hand

WARNINGS

1.Keep out of reach of children.

2.Store in a cool, dry place and avoid direct sunlight.

3.If abnormal symptoms occur after use, stop use and consult with a skin specialist.

DOSAGE AND ADMINISTRATION

for external use only